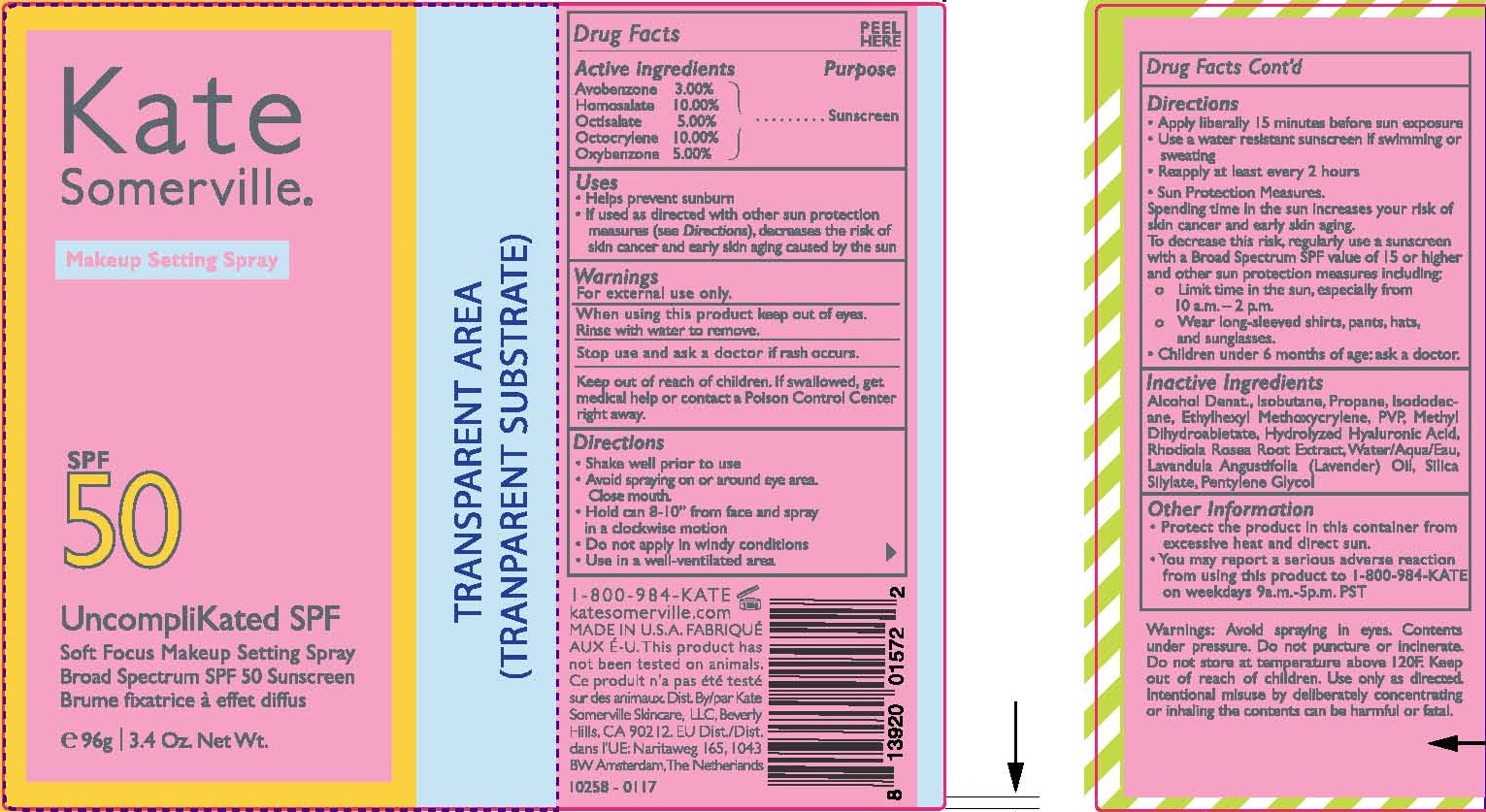 DRUG LABEL: UNCOMPLIKATED MAKEUP SETTING
NDC: 72204-904 | Form: AEROSOL, SPRAY
Manufacturer: Rare Beauty Brands Inc.
Category: otc | Type: HUMAN OTC DRUG LABEL
Date: 20251201

ACTIVE INGREDIENTS: AVOBENZONE 3 g/100 g; HOMOSALATE 10 g/100 g; OCTISALATE 5 g/100 g; OCTOCRYLENE 10 g/100 g; OXYBENZONE 5 g/100 g
INACTIVE INGREDIENTS: ISOBUTANE; PROPANE; ISODODECANE; ETHYLHEXYL METHOXYCRYLENE; POVIDONE, UNSPECIFIED; METHYL DIHYDROABIETATE; HYALURONIC ACID; RHODIOLA ROSEA ROOT; WATER; LAVENDER OIL; SILICA, TRIMETHYLSILYL CAPPED; PENTYLENE GLYCOL; ALCOHOL

KATE SOMERVILLE (as PLD) - UNCOMPLIKATED MAKEUP SETTING SPRAY SPF 50 (43479-208)

ACTIVE INGREDIENTS

AVOBENZONE 3.00%

HOMOSALATE 10.00%

OCTISALATE 5.00%

OCTOCRYLENE 10.00%

OXYBENZONE 5.00%

PURPOSE

SUNSCREEN

USES

- HELPS PREVENT SUNBURN.
- IF USED AS DIRECTED WITH OTHER SUN PROTECTION MEASURES (SEE DIRECTIONS) DECREASES THE RISK OF SKIN CANCER AND EARLY SKIN AGING CAUSED BY THE SUN.

WARNINGS

FOR EXTERNAL USE ONLY

WHEN USING THIS PRODUCT, KEEP OUT OF EYES.

RINSE WITH WARM WATER TO REMOVE.

STOP USE AND ASK A DOCTOR IF RASH OCCURS.

KEEP OUT OF REACH OF CHILDREN. IF PRODUCT IS SWALLOWED, GET MEDICAL HELP OR CONTACT A POISON CONTROL CENTER RIGHT AWAY.

DOSAGE AND ADMINISTRATION

- SHAKE WELL PRIOR TO USE.
- AVOID SPRAYING ON OR AROUND EYE AREA. CLOSE MOUTH.
- HOLD CAN 8-10" FROM FACE AND SPRAY IN A CLOCKWISE DIRECTION.
- DO NOT APPLY IN WINDY CONDITIONS.
- USE IN A WELL-VENTILATED AREA.
- APPLY LIBERALLY 15 MINUTES BEFORE SUN EXPOSURE.
- USE A WATER RESISTANT SUNSCREEN IF SWIMMING OR SWEATING.
- REAPPLY AT LEAST EVERY 2 HOURS.

- SUN PROTECTION MEASURES.
  SPENDING TIME IN THE SUN INCREASES YOUR RISK OF SKIN CANCER AND EARLY SKIN AGING. TO DECREASE THIS RISK, REGULARLY USE A SUNSCREEN WITH A BROAD SPECTRUM SPF VALUE OF 15 OR HIGHER AND OTHER SUN PROTECTION MEASURES INCLUDING:

LIMIT TIME IN THE SUN, ESPECIALLY FROM 10 A.M.-2 P.M.

WEAR LONG-SLEEVED SHIRTS, PANTS, HATS, AND SUNGLASSES.

- CHILDREN UNDER 6 MONTHS: ASK A DOCTOR.

OTHER INFORMATION

- PROTECT THIS PRODUCT FROM EXCESSIVE HEAT AND DIRECT SUN.
- YOU MAY REPORT A SERIOUS ADVERSE REACTION FROM USING THIS PRODUCT TO 1-800-984-KATE ON WEEKDAYS 9 A.M.-5 P.M. PST.

INACTIVE INGREDIENTS

ALCOHOL DENAT., ISOBUTANE, PROPANE, ISODODECANE, ETHYLHEXYL METHOXYCRYLENE, PVP, METHYL DIHYDROABIETATE, HYDROLYZED HYALURONIC ACID, RHODIOLA ROSEA ROOT EXTRACT, KATER/AQUA/EAU, LAVANDULA ANGUSTIFOLIA (LAVENDER) OIL, SILICA SILYLATE, PENTYLENE GLYCOL